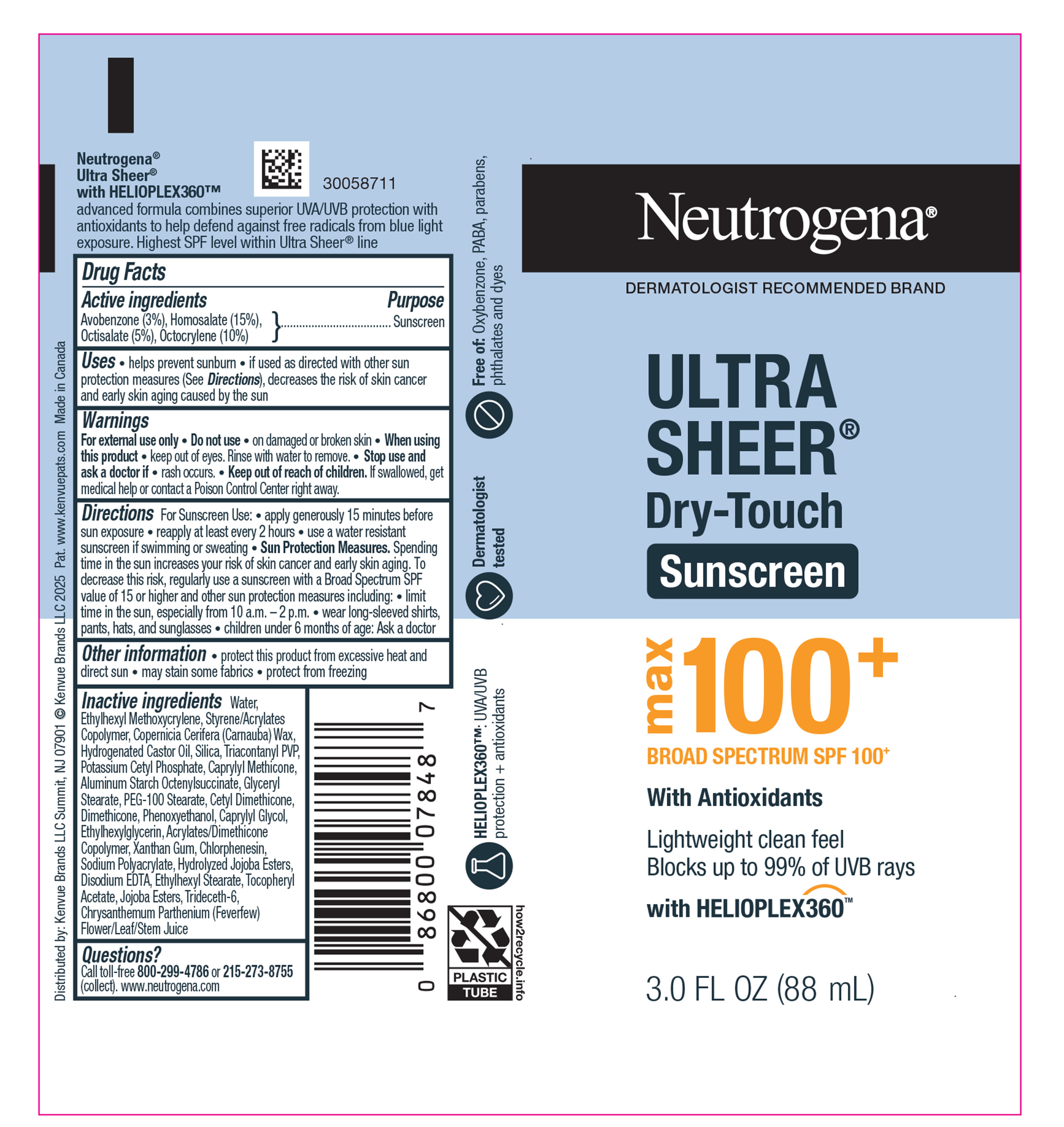 DRUG LABEL: Neutrogena Ultra Sheer Dry-Touch Sunscreen MAX Broad Spectrum SPF 100 Plus
NDC: 69968-0936 | Form: LOTION
Manufacturer: Kenvue Brands LLC
Category: otc | Type: HUMAN OTC DRUG LABEL
Date: 20250806

ACTIVE INGREDIENTS: AVOBENZONE 30 mg/1 mL; OCTOCRYLENE 100 mg/1 mL; HOMOSALATE 150 mg/1 mL; OCTISALATE 50 mg/1 mL
INACTIVE INGREDIENTS: BUTYL METHACRYLATE/METHYL METHACRYLATE/METHACRYLIC ACID/STYRENE CROSSPOLYMER; HYDROGENATED CASTOR OIL; 2-ETHYLHEXYL ACRYLATE, METHACRYLATE, METHYL METHACRYLATE, OR BUTYL METHACRYLATE/HYDROXYPROPYL DIMETHICONE COPOLYMER (30000-300000 MW); ETHYLHEXYLGLYCERIN; WATER; TRIACONTANYL PVP; DIMETHICONE; TRIDECETH-6; XANTHAN GUM; JOJOBA OIL, RANDOMIZED; GLYCERYL STEARATE; PEG-100 STEARATE; PHENOXYETHANOL; POTASSIUM CETYL PHOSPHATE; CETYL DIMETHICONE 25; ALPHA-TOCOPHEROL ACETATE; ALUMINUM STARCH OCTENYLSUCCINATE; CAPRYLYL GLYCOL; EDETATE DISODIUM; TANACETUM PARTHENIUM WHOLE; ETHYLHEXYL METHOXYCRYLENE; CHLORPHENESIN; ETHYLHEXYL STEARATE; SILICA; HYDROLYZED JOJOBA ESTERS; COPERNICIA CERIFERA (CARNAUBA) WAX; CAPRYLYL METHICONE

Neutrogena Ultra Sheer Dry-Touch Sunscreen MAX Broad Spectrum SPF 100 Plus

Drug Facts

Active ingredients

Avobenzone (3%), Homosalate (15%),

Octisalate (5%), Octocrylene (10%)

Purpose

Sunscreen

Uses

- helps prevent sunburn
- if used as directed with other sun protection measures (See Directions), decreases the risk of skin cancer and early skin aging caused by the sun

Warnings

For external use only

• Do not use • on damaged or broken skin

• When using this product • keep out of eyes. Rinse with water to remove.

● Stop use and ask a doctor if ● rash occurs.

● Keep out of reach of children. If swallowed, get medical help or contact a Poison Control Center right away.

Directions

For Sunscreen Use:

● apply generously 15 minutes before sun exposure

● reapply at least every 2 hours

● use a water resistant sunscreen if swimming or sweating

● Sun Protection Measures. Spending time in the sun increases your risk of skin cancer and early skin aging. To decrease this risk, regularly use a sunscreen with a Broad Spectrum SPF value of 15 or higher and other sun protection measures including:

● limit time in the sun, especially from 10 a.m. – 2 p.m.

● wear long-sleeved shirts, pants, hats, and sunglasses

● children under 6 months of age: Ask a doctor

Other information

- protect this product from excessive heat and direct sun
- may stain some fabrics
- protect from freezing

Inactive ingredients

Water, Ethylhexyl Methoxycrylene, Styrene/Acrylates Copolymer, Copernicia Cerifera (Carnauba) Wax, Hydrogenated Castor Oil, Silica, Triacontanyl PVP, Potassium Cetyl Phosphate, Caprylyl Methicone, Aluminum Starch Octenylsuccinate, Glyceryl Stearate, PEG-100 Stearate, Cetyl Dimethicone, Dimethicone, Phenoxyethanol, Caprylyl Glycol, Ethylhexylglycerin, Acrylates/Dimethicone Copolymer, Xanthan Gum, Chlorphenesin, Sodium Polyacrylate, Hydrolyzed Jojoba Esters, Disodium EDTA, Ethylhexyl Stearate, Tocopheryl Acetate, Jojoba Esters, Trideceth-6, Chrysanthemum Parthenium (Feverfew) Flower/Leaf/Stem Juice

Questions?

Call toll-free 800-299-4786 or 215-273-8755 (collect). www.neutrogena.com

Distributed by:

Kenvue Brands LLC

Summit, NJ 07901

PRINCIPAL DISPLAY PANEL - 88 mL Tube Label

Neutrogena®

DERMATOLOGIST RECOMMENDED BRAND

ULTRA

SHEER®

Dry-Touch

Sunscreen

max

100+

BROAD SPECTRUM SPF 100+

With Antioxidants

Lightweight clean feel

Blocks up to 99% of UVB rays

with HELIOPLEX360TM

3.0 FL OZ (88 mL)